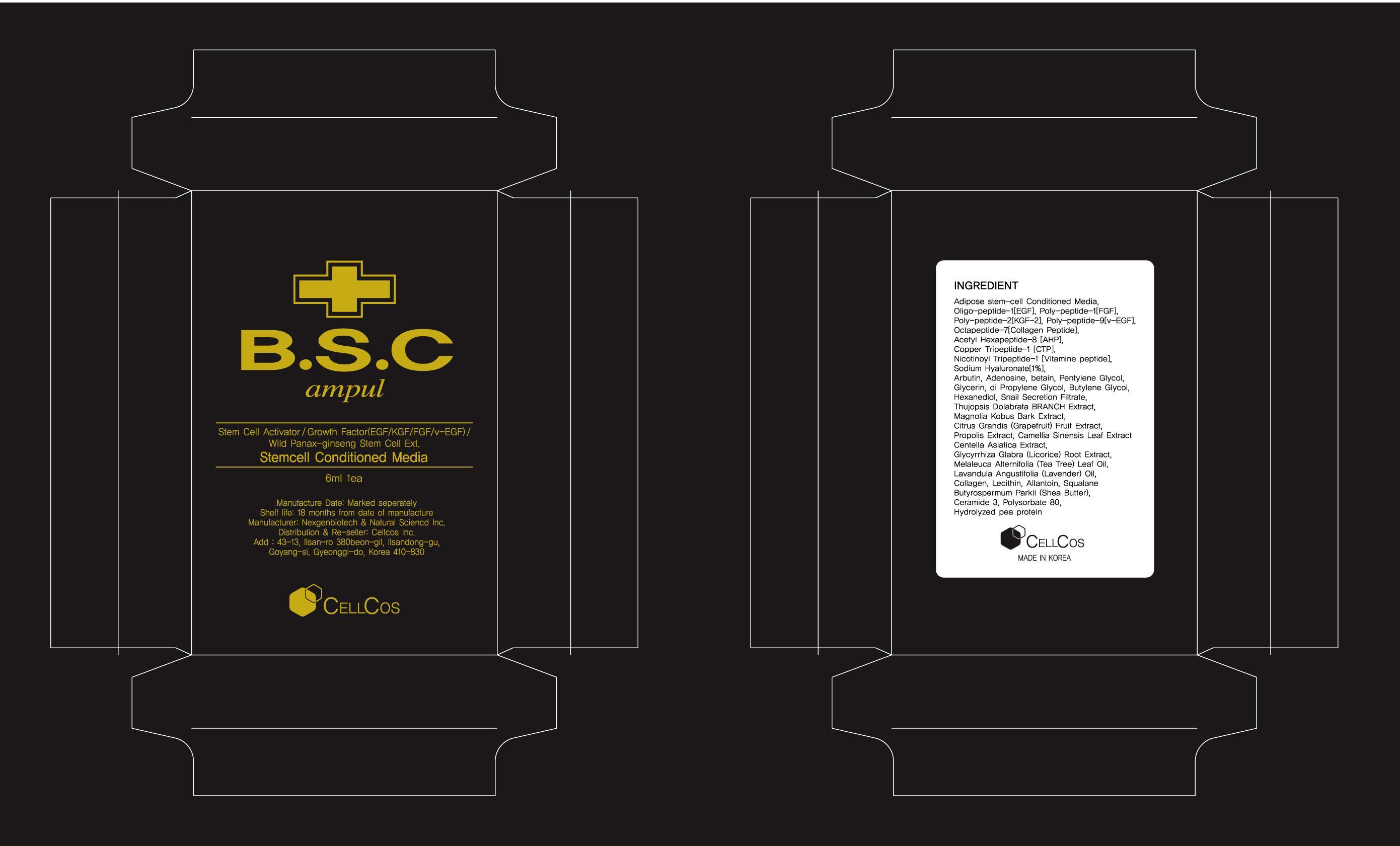 DRUG LABEL: B.S.C AMPUL
NDC: 55502-1001 | Form: LIQUID
Manufacturer: Cellcos Inc
Category: otc | Type: HUMAN OTC DRUG LABEL
Date: 20130130

ACTIVE INGREDIENTS: ADENOSINE 0.6 mg/6 mL
INACTIVE INGREDIENTS: HUMAN ADIPOSE; PANAX GINSENG WHOLE; ACETYL HEXAPEPTIDE-8; PREZATIDE COPPER; PREZATIDE; HYALURONATE SODIUM; LECITHIN, SOYBEAN; ALLANTOIN; HEXANEDIOL; GLYCERIN; DIPROPYLENE GLYCOL; BUTYLENE GLYCOL; BETAINE; PENTYLENE GLYCOL; ARBUTIN; SNAIL, UNSPECIFIED; THUJOPSIS DOLABRATA WHOLE; MAGNOLIA KOBUS BARK; PUMMELO; PROPOLIS WAX; TEA LEAF OIL; CENTELLA ASIATICA; GLYCYRRHIZA GLABRA; MELALEUCA ALTERNIFOLIA LEAF; LAVANDULA ANGUSTIFOLIA FLOWERING TOP; SQUALANE; SHEA BUTTER; CERAMIDE 3; POLYSORBATE 80; PEA PROTEIN

Drug Facts

ACTIVE INGREDIENT

adenosine

INACTIVE INGREDIENT

Adipose Stem-cell Conditioned Media,Mt.Panax ginseng Stemcell[callus] peptide-1[EGF], Poly-peptide-1[FGF], Poly-peptide-2[KGF], Poly-peptide-9[v-EGF], Oligo- Octapeptide-7[Collagen Peptide] Acetyl Hexapeptide-8 [AHP] Copper Tripeptide-1 [CTP] Nicotinoyl Tripeptide-1[Vitamine peptide] Collagen,Sodium Hyaluronate,Arbutin,Adenosine Lecithin Allantoin Hexanediol Caster oil, Glycerin Dipropylene Glycol Butylene Glycol Snail Secretion Filtrate Cabopol XanthanGum Triethanolamine Salix Alba (Willow) Bark Extract
Red Ginseng Extract,Panax Ginseng Root Extract Panax Ginseng Root Extract Thujopsis Dolabrata BRANCH Extract Magnolia Kobus Bark Extract Citrus Grandis (Grapefruit) Fruit Extract Camellia Sinensis Leaf Extract Centella Asiatica Extract Propolis Extract Glycyrrhiza Glabra (Licorice) Root Extract Chamomilla Recutita (Matricaria) Flower Extract Rosmarinus Officinalis (Rosemary) Extract Polygonum Cuspidatum Root Extract Scutellaria Baicalensis Root Extract Hydrolyzed Pea Protein Platycodon Grandiflorum Root Extract Bupleurum Chinensis Root Extract ,Bupleurum Falcatum Root Extract Dioscorea Japonica Root Extract Zizyphus Jujuba Fruit Extract Atractyloides Japonica Rhizome Extract Atractyloides Macrocephala Root Extract Forsythia Suspensa Fruit Extract Cnidium Officinale Root Extract ,Cnidium Officinale Rhizome Extract Codonopsis Lanceolata Root Extract Scutellaria Baicalensis Root Extract Schizonepeta Tenuifolia Extract Morus Alba Bark Extract Souhakuhi Ekisu Gardenia Florida Fruit Extract,Gardenia Jasminoides Fruit Extract Glycyrrhiza Glabra (Licorice) Root Extract Glycyrrhiza Uralensis (Licorice) Root Extract Glycyrrhiza Inflata Root Extract Angelica Dahurica Root Extract Lonicera Japonica (Honeysuckle) Flower Extract Citrus Unshiu Peel Extract Poria Cocos Extract,Poria Cocos Sclerotium Extract Angelica Gigas Root Extract Paeonia Albiflora Root Extract ,Paeonia Lactiflora Root Extract Astragalus Membranaceus Root Extract Melaleuca Alternifolia (Tea Tree) Leaf Oil Lavandula Angustifolia (Lavender) Oil Lemon Oil.

PURPOSE

skin whitening and lifting

keep out or reach of the children

INDICATIONS AND USAGE

after toner cover your face
wait for 20 minutes

WARNINGS

1.Avoid using on blemishes, pimples, irritated or sunburned skin.
2. Stop using if skin becomes red, swollen, and itchy during and after use.
3. If pain persists after make is peeled off and above sings occur, discontinue immediately and consult your doctor.
4. Avoid contact with the eyes. If contact occurs, rinse eyes thoroughly with water.

DOSAGE AND ADMINISTRATION

for external use only